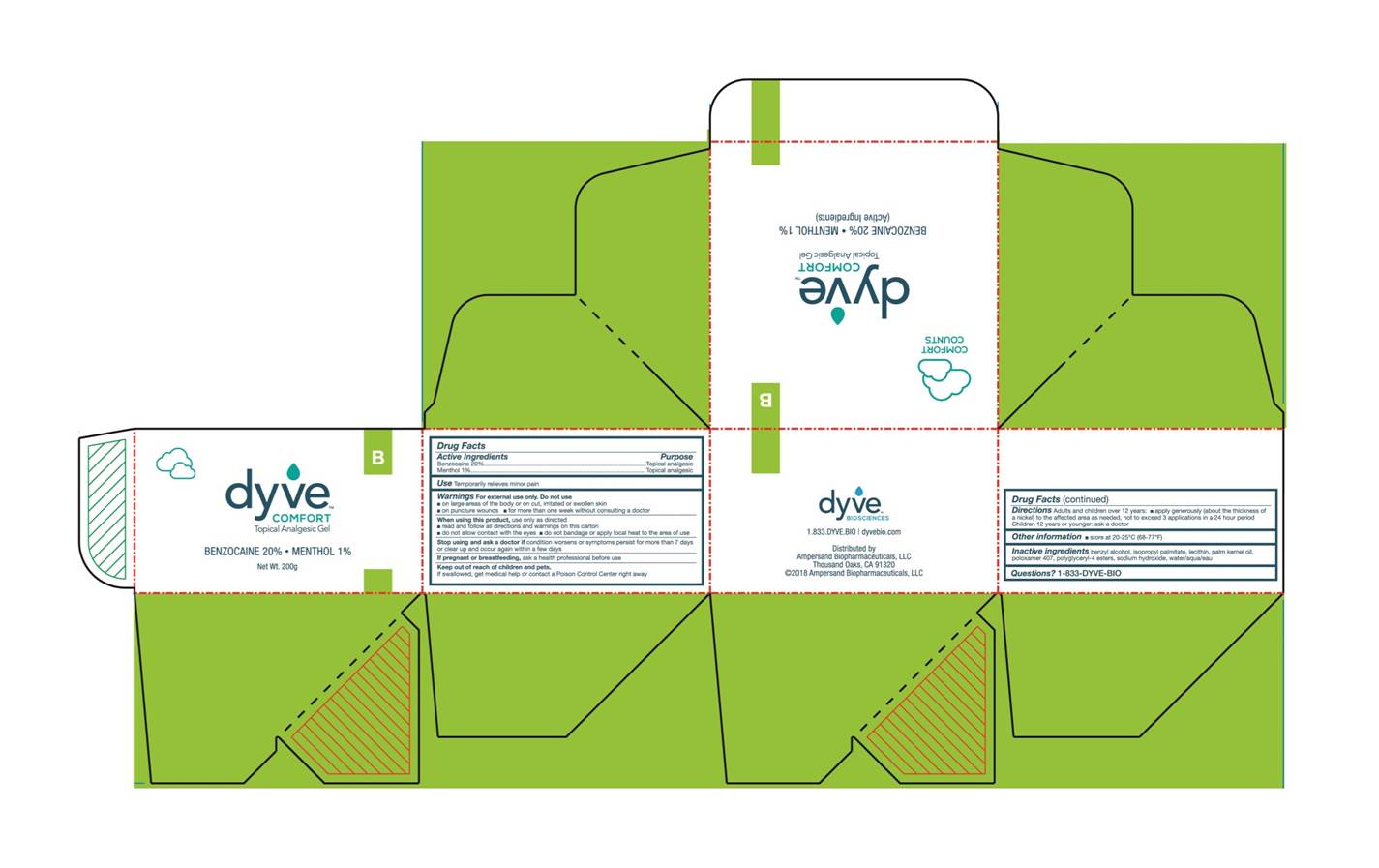 DRUG LABEL: Dyve Comfort B
NDC: 70458-104 | Form: GEL
Manufacturer: AmperSand Biopharmaceuticals
Category: otc | Type: HUMAN OTC DRUG LABEL
Date: 20180321

ACTIVE INGREDIENTS: MENTHOL 1 g/100 g; BENZOCAINE 20 g/100 g
INACTIVE INGREDIENTS: ISOPROPYL PALMITATE; LECITHIN, SOYBEAN; POLOXAMER 407; BENZYL ALCOHOL; WATER; POLYGLYCERYL-4 STEARATE; PALM KERNEL OIL; POLYGLYCERYL-4 OLEATE; SODIUM HYDROXIDE

Active Ingredients

Benzocaine 20%

Menthol 1%

Purpose

Topical analgesic

Uses

Temporarily relieves minor pain

Warnings

For external use only

Do not use

On large areas of the body or on cut, irritated or swollen skin
On puncture wounds
For more than one week without consulting a doctor

When using this product:

Use only as directed

Read and follow all direction and warnings on this carton

Do not allow contact with eyes

Do not bandage or apply local heat to the area of use

Stop using and ask a doctor if

Condition worsens or symptoms persist for more than 7 days or clear up and occur again within a few days

If pregnant or breastfeeding,

ask a health professional before use

Keep out of reach of children and pets.

If swallowed, get medical help or contact a Poison Control Center right away

Directions

Adults and children over 12 years: Apply generously (about the thickness of a nickel) to the affected area as needed, not to exceed 3 applications in a 24 hour period. Children 12 years or younger: ask a doctor

Other information

Store at 20-25ºC (68-77ºF)

Inactive ingredients

benzyl alcohol, isopropyl palmitate, lecithin, palm kernel oil, poloxamer 407, polyglyceryl-4 esters, sodium hydroxide, water

Questions?

1-833-DYVE-BIO